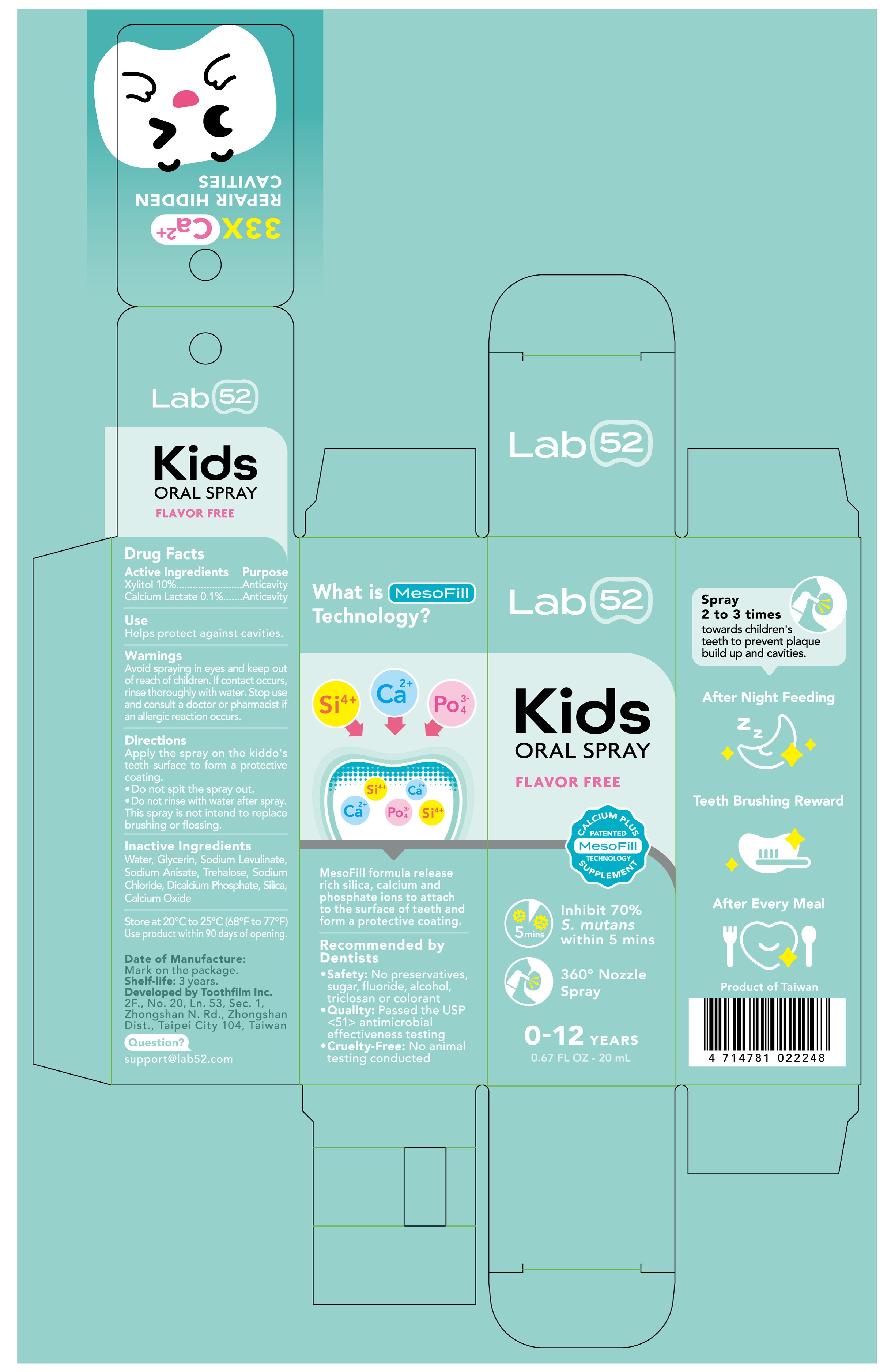 DRUG LABEL: Kids Oral Care Flavor Free
NDC: 82711-106 | Form: SPRAY
Manufacturer: TOOTHFILM INC.
Category: otc | Type: HUMAN OTC DRUG LABEL
Date: 20250421

ACTIVE INGREDIENTS: CALCIUM LACTATE 0.02 mg/20 mg; XYLITOL 2 mg/20 mg
INACTIVE INGREDIENTS: SODIUM ANISATE; SODIUM LEVULINATE; SODIUM CHLORIDE; CALCIUM OXIDE; GLYCERIN; WATER; SILICA; DICALCIUM PHOSPHATE; TREHALOSE

Kids Oral Care Flavor Free

ACTIVE INGREDIENT

Active ingredients: Xylitol 2.0mL/20mL; Calcium Lactate 0.02mL/20mL

INACTIVE INGREDIENT

Inactive ingredients: Water, Glycerin, Sodium Levulinate, Sodium Anisate, Trehalose, Sodium Chloride, Dicalcium Phosphate, Silica, Calcium Oxide

Purpose: Anticavity

keep out of reach of children: For external use only. Keep out of reach of children. Avoid contact with eyes. Discontinue use if signs of irritation or rash occur.

INDICATIONS AND USAGE

Spray after meals and feedings. Don’t forget to brush kid's teeth for the best results! It’s fluoride-free, preservative-free, and safe to swallow when used as directed!

Apply the spray on the kiddo's teeth surface to form a protective coating. • Do not spit the spray out. • Do not rinse with water after spray. This spray is not intend to replace brushing or flossing.

WARNINGS

Warnings: Avoid spraying in eyes. In case of contact, rinse eyes thoroughly with water. Stop use and ask a doctor or pharmacist if you have an allergic reaction to this product or any of its ingredients.

DOSAGE AND ADMINISTRATION

Helps protect against cavities. Spray 2 to 3 times towards children's teeth to prevent plaque build up and cavities.

QUESTIONS

Question: support@lab52.com

OTHER SAFETY INFORMATION

Other: Store at 20°C to 25°C (68°F to 77°F) Use product within 90 days of opening.

See Label